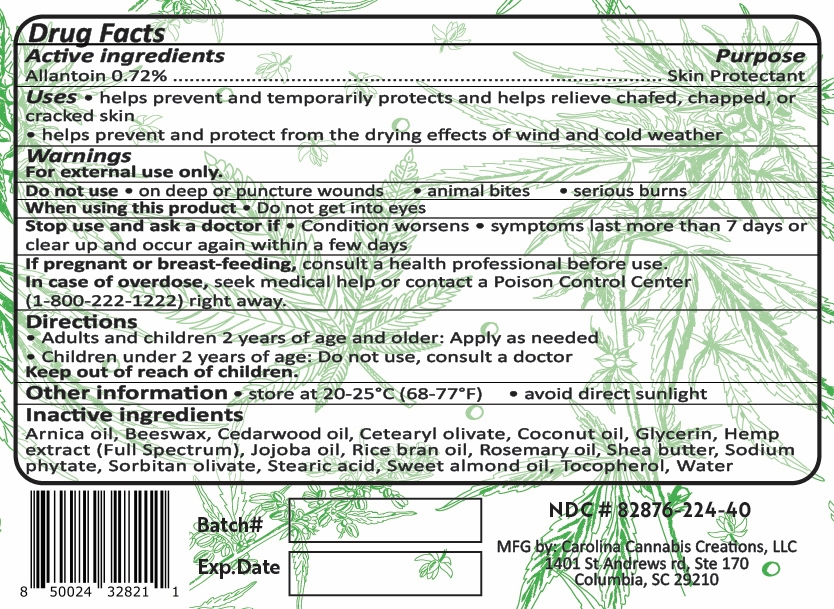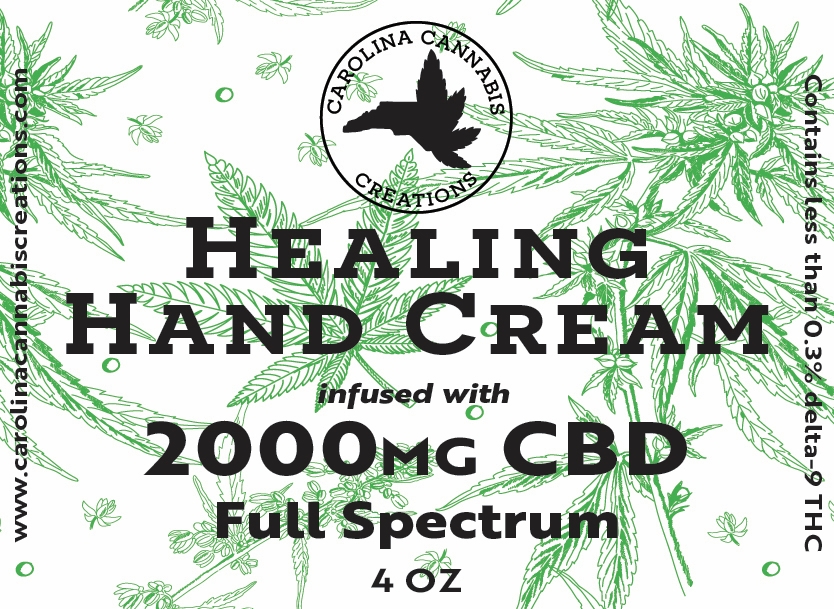 DRUG LABEL: Healing Hand Cream
NDC: 82876-224 | Form: CREAM
Manufacturer: Carolina Cannabis Creations LLC
Category: otc | Type: HUMAN OTC DRUG LABEL
Date: 20250902

ACTIVE INGREDIENTS: ALLANTOIN 0.85 g/118.76 g
INACTIVE INGREDIENTS: COCONUT OIL 2.21 g/118.76 g; BENZYL ALCOHOL 0.85 g/118.76 g; GLYCERIN 6.65 g/118.76 g; BEEF TALLOW 2.42 g/118.76 g; XANTHAN GUM 0.34 g/118.76 g; STEARIC ACID 1.1 g/118.76 g; DEHYDROACETIC ACID 0.08 g/118.76 g; JOJOBA OIL 2.21 g/118.76 g; PEG-8 BEESWAX 1.11 g/118.76 g; ALMOND OIL 1.11 g/118.76 g; CETEARYL OLIVATE 2.664 g/118.76 g; ROSEMARY OIL 0.66 g/118.76 g; RICE BRAN OIL 4.44 g/118.76 g; SHEA BUTTER 1.11 g/118.76 g; CANNABIDIOL 2.7 g/118.76 g; ARNICA MONTANA FLOWER WATER 2.1 g/118.76 g; SODIUM PHYTATE 0.11 g/118.76 g; WATER 83.07 g/118.76 g; CEDRUS ATLANTICA WOOD OIL 0.44 g/118.76 g; TOCOPHEROL 0.66 g/118.76 g; SORBITAN OLIVATE 1.776 g/118.76 g

CCC Healing Hand Cream

Active Ingredients

Allantoin 0.72% .................................................................................................. Skin Protectant

Purpose

Allantoin 0.72% .................................................................................................. Skin Protectant

Uses

helps prevent and temporarily protects and helps relieve chafed, chapped, or
cracked skin • helps prevent and protect from the drying effects of wind and cold weather

Warnings

FOR EXTERNAL USE ONLY.

When using this product

Do not get into eyes

DO NOT USE

on deep or puncture wounds • animal bites • serious burns

Stop use and ask a doctor if

The condition worsens, symptoms last more than 7 days, the condition clears but occurs again within a few days.

Stop use and ask a doctor if

Condition worsens, Symptoms last more than 7 days, Condition clears up but occurs again within a few days.

If pregnant or breastfeeding

Consult a health professional before use

In case of an overdose

seek medical help or contact a poison control center right away

Directions

• Adults and children 2 years of age and older: Apply as needed
• Children under 2 years of age: Do not use, consult a doctor

Keep out of reach of children

Keep out of reach of children

Other information

Store at 68-77 degrees F, Avoid direct sunlight

Inactive ingredients

Arnica oil, Beeswax, Cedarwood oil, Cetearyl olivate, Coconut oil, Glycerin, Hemp
extract (Full Spectrum), Jojoba oil, Rice bran oil, Rosemary oil, Shea butter, Sodium
phytate, Sorbitan olivate, Stearic acid, Sweet almond oil, Tocopherol, Water